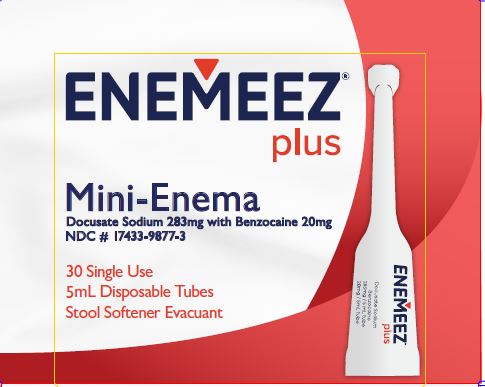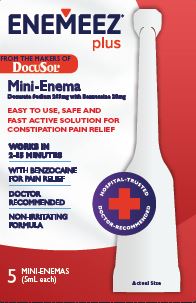 DRUG LABEL: ENEMEEZ Plus
NDC: 17433-9877 | Form: LIQUID
Manufacturer: Quest Products, LLC
Category: otc | Type: HUMAN OTC DRUG LABEL
Date: 20250715

ACTIVE INGREDIENTS: DOCUSATE SODIUM 283 mg/5 mL; BENZOCAINE 20 mg/5 mL
INACTIVE INGREDIENTS: POLYETHYLENE GLYCOL 300; GLYCERIN

Enemeez® Plus

Drug Facts

Active ingredient (per mini enema)

Docusate Sodium USP 283 mg

Benzocaine 20mg

PURPOSE

Docusate Sodium USP 283 mg ............. Stool Softener Laxative

Benzocaine 20mg ................................ Anesthetic

Uses

For relief of occasional constipation (irregularity). This product generally produces a stimulus and bowel movement in 2 to 15 minutes.

Warnings

For rectal use only. This is not a suppository. Do not take orally. Individuals with sensitivity to Benzocaine should not use this product.

Ask a doctor before use if you have:

- abdominal pain, nausea or vomiting.
- a sudden change in bowel habits that persists over a period of 2 weeks.

Ask a doctor or pharmacist before use if you are presently taking mineral oil.

Stop use and ask a doctor if you:

- have rectal bleeding.
- failed to have a bowel movement after use. This may indicate a serious condition.
- encounter resistance. Forcing the tube may result in injury or damage to the rectum. If product is not administered properly and occasional rectal examinations are not performed, serious complications can arise. Occasional rectal exams are imperative for patients with impaired rectal function, especially loss of sensation.
- require a bowel program for longer than 1 week.
- experience rectal irritation or a rash around the anus appears.

PREGNANCY OR BREAST FEEDING

If pregnant or breast-feeding, ask a health professional before use.

Keep out of reach of children.

OVERDOSAGE

In case of accidental ingestion or overdose, get medical help or contact a Poison Control Center immediately.

Directions

Adults and children 12 years of age and older (with adult supervision) one to three units daily. Children 2 years and over but not more than 12 years should consult a doctor prior to use and not exceed one unit daily (with adult supervision).

Twist off and remove tip; Lubricate tip prior to insertion: Place a few drops of water or product on the shaft prior to insertion. Also apply one of these lubricants to the anus before inserting the enema. With steady pressure, gently insert the tube into the rectum with care to prevent damage to the rectal wall. Squeeze to empty the contents. Continue squeezing the tube until it is removed from the rectum. Remove the disposable tube and discard. A small amount of liquid may remain in the tube after use.

Positioning:
For best results, lay on the left side with knees bent.

Alternate Positions:

- Administer while seated on the toilet.
- Kneel with the left arm folded comfortably, then lower head and chest forward until side of face is resting on the surface.

Other Information

Other Information Store at room temperature 15°-30° C (59°-86° F)

Inactive Ingredients

Inactive Ingredients Polyethylene Glycol and Glycerin USP

Questions or Comments: 1-888-273-9734 or www.enemeez.com

Manufactured by:
Enemeez, Inc., Phoenix, AZ 85050

Distributed by:
Alliance Labs, L.L.C
2515 E. Rose Garden Lane, Suite #1
Phoenix, AZ 85050